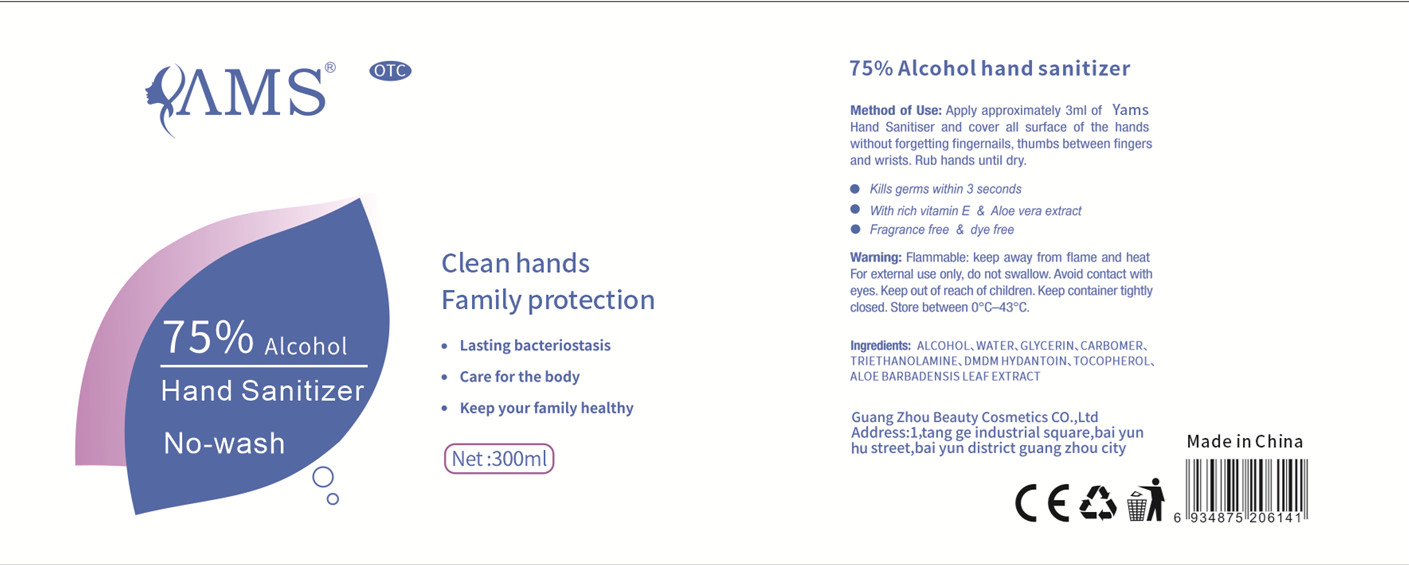 DRUG LABEL: 75% Alcohol Hand Sanitizer
NDC: 40303-002 | Form: GEL
Manufacturer: Guangzhou Beauty Cosmetics Co., Ltd.
Category: otc | Type: HUMAN OTC DRUG LABEL
Date: 20200421

ACTIVE INGREDIENTS: ALCOHOL 225 mL/300 mL
INACTIVE INGREDIENTS: GLYCERIN; WATER; CARBOMER COPOLYMER TYPE A (ALLYL PENTAERYTHRITOL CROSSLINKED); TROLAMINE; ALOE VERA LEAF; DMDM HYDANTOIN; TOCOPHEROL

DOSAGE AND ADMINISTRATION

Store below 30 °C

INACTIVE INGREDIENT

ALCOHOL

WATER

GLYCERIN

CARBOMER

TRIETHANOLAMINE

DMDM HYDANTOIN

TOCOPHEROL

ALOE BARBADENSIS LEAF EXTRACT

INDICATIONS AND USAGE

For external use, take a proper amount and rub your hands for disinfection. The action time is 1 minute.

ACTIVE INGREDIENT

ALCOHOL

keep out of children

PURPOSE

Disinfection
Sterilization
No Rinseing

WARNINGS

1. Topical disinfection gel, avoid oral administration;
2. Keep it out of reach of children;
3. Flammable and should keep it away from fire sources.